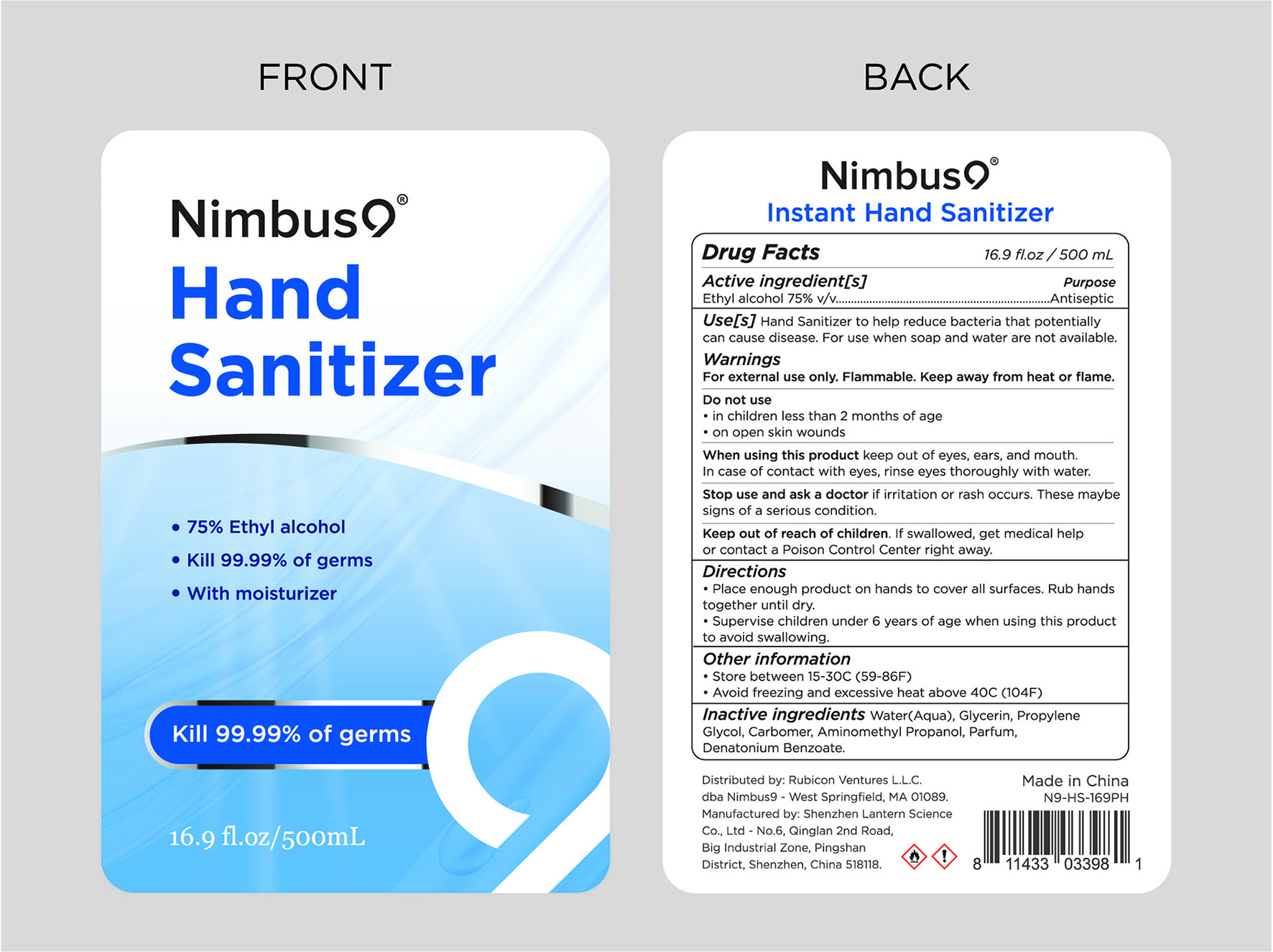 DRUG LABEL: Nimbus9  hand sanitizer 500ml
NDC: 54860-290 | Form: LIQUID
Manufacturer: Shenzhen Lantern Scicence Co.,Ltd.
Category: otc | Type: HUMAN OTC DRUG LABEL
Date: 20200623

ACTIVE INGREDIENTS: ALCOHOL 75 mL/100 mL
INACTIVE INGREDIENTS: DENATONIUM BENZOATE 0.00054 mL/100 mL; CARBOMER 940 0.35 mL/100 mL; PROPYLENE GLYCOL 0.01 mL/100 mL; AMINOMETHYLPROPANOL 0.11 mL/100 mL; WATER 24.41946 mL/100 mL; GLYCERIN 0.01 mL/100 mL; LEMON 0.1 mL/100 mL

Nimbus9 hand sanitizer 500ml

Active Ingredient

Active Ingredient Purpose

Ethyl Alcohol 75%（v/v） Antiseptic

USE

Hand sanitizer to help reduce bacteria that potentially can cause disease.For use when soap and water are not available.

DOSAGE AND ADMINISTRATION

Recommended for repeated use.

use anywhere without water.

Warning

For external use only.Flammable.Keep away from heat or flame.

WARNINGS AND PRECAUTIONS

For external use only.

Flammable, keep away from heat and flame.

STOP USE

Discontinue if skin becomes irritated and ask a doctor .

Keep out of reach of children. In case of accidental ingestion, seek professional assistance or contact a poson control center immediately.

Inactive ingredients

Water, Glycerin,propylene Glycol,carbomer,Aminomethyl propanol,Parfum,Denatonium benzoate.

Directions

Place enough product on hands to cover all surfaces,Rub hands together until dry.

Supervise children under 6 years of age when using this product to avoid swallowing.

When using this product

keep out of eyes. In case of contact with eyes, flush thoroughly with water.

Do not inhale or ingest.

Avoid contact with broken skin.

Other information

Do not store above 105F.

May discolor some fabrics.

Harmful to wood finishes and plastics.

Other information

Store between 15-30℃（59-86F）

Avoid freezing and excessive heat above 40℃（104F）

Do not use

in children less than 2 months of age

on open skin wounds

When using this product

Keep out of eyes,ears,and mouth.In case of contact with eyes.rinse eyes thoroughly with water.

Stop use an ask a doctor

if irritation or rash occurs,these maybe signs of a serious condition.

Keep out of reach of children

if swallowed,get medical help or contact a Poison Control Center right away.